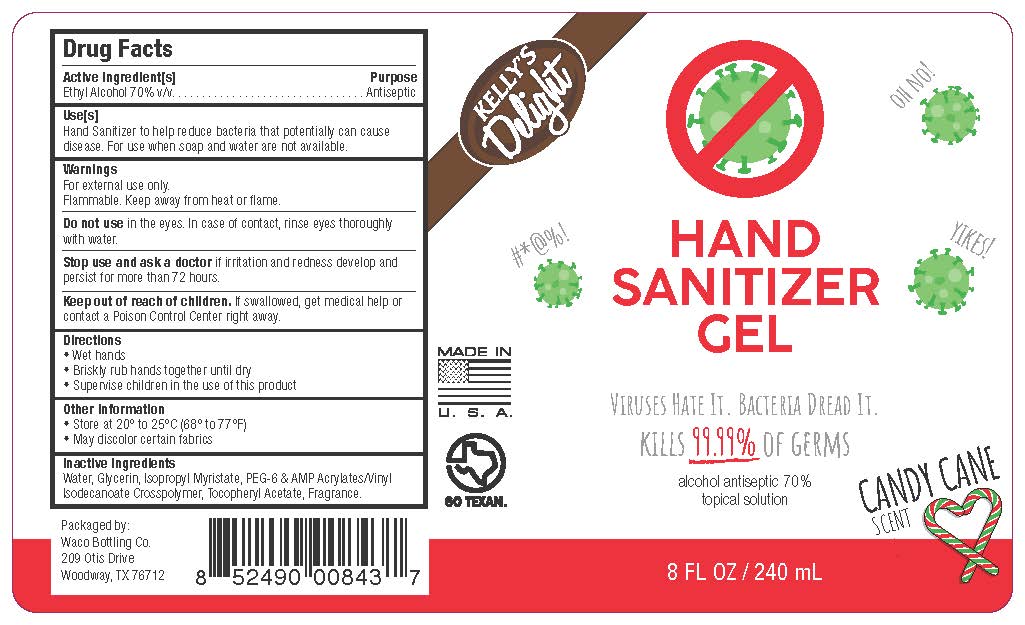 DRUG LABEL: Kellys Delight Hand Sanitizer

NDC: 79175-013 | Form: GEL
Manufacturer: WACO BOTTLING LLC
Category: otc | Type: HUMAN OTC DRUG LABEL
Date: 20221114

ACTIVE INGREDIENTS: ALCOHOL 70 mL/100 mL
INACTIVE INGREDIENTS: WATER; POLYETHYLENE GLYCOL 300; ACRYLATES/VINYL ISODECANOATE CROSSPOLYMER (10000 MPA.S NEUTRALIZED AT 0.5%); GLYCERIN; ISOPROPYL MYRISTATE; ALPHA-TOCOPHEROL ACETATE; DIPROPYLENE GLYCOL; PEPPERMINT OIL; MENTHA ARVENSIS FLOWER OIL; ETHYL VANILLIN

Active Ingredient

Ethyl Alcohol 70% v/v.

Purpose

Antiseptic

Use

Hand Sanitizer to help reduce bacteria that potentially can cause disease.

For use when soap and water are not available.

Warnings

For external use only.

Flammable. Keep away from heat or flame.

Do not use in the eyes. In case of contact, rinse eyes thoroughly with water.

Stop use and ask a doctor if irritation and redness develop and persist for more than 72 hours.

Keep out of reach of children. If swallowed, get medical help or contact a Poison Control Center right away.

Directions

•Wet hands.

•Briskly rub hands together until dry.

•Supervise children in the use of this product.

Other Information

•Store at 20-25C(68-77F)

•Avoid freezing and excessive heat above 40C (104F)

Inactive Ingredients

Water, Glycerin, Isopropyl Myristate, PEG-6 & AMP Acrylates/Vinyl Isodecanoate Crosspolymer, Tocopheryl Acetate, Fragrance.